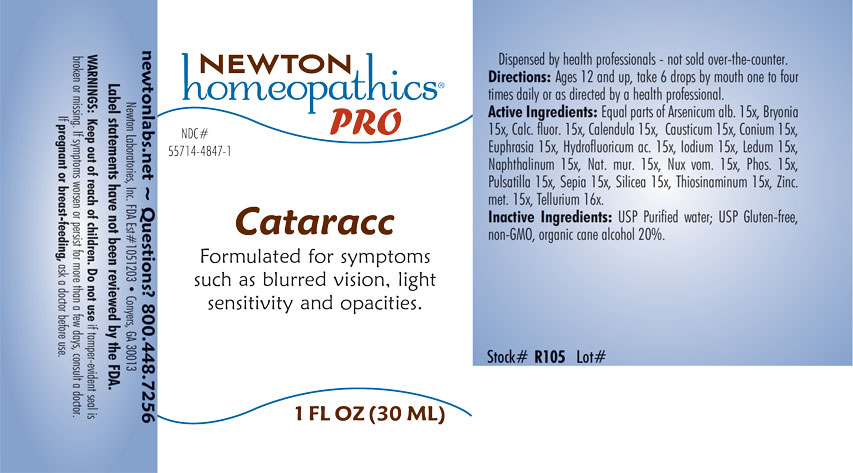 DRUG LABEL: Cataracc
NDC: 55714-4847 | Form: LIQUID
Manufacturer: Newton Laboratories, Inc.
Category: homeopathic | Type: HUMAN OTC DRUG LABEL
Date: 20221216

ACTIVE INGREDIENTS: HYDROFLUORIC ACID 15 [hp_X]/1 mL; SODIUM CHLORIDE 15 [hp_X]/1 mL; CALENDULA OFFICINALIS FLOWERING TOP 15 [hp_X]/1 mL; CAUSTICUM 15 [hp_X]/1 mL; CALCIUM FLUORIDE 15 [hp_X]/1 mL; IODINE 15 [hp_X]/1 mL; ALLYLTHIOUREA 15 [hp_X]/1 mL; RHODODENDRON TOMENTOSUM LEAFY TWIG 15 [hp_X]/1 mL; EUPHRASIA STRICTA 15 [hp_X]/1 mL; CONIUM MACULATUM FLOWERING TOP 15 [hp_X]/1 mL; NAPHTHALENE 15 [hp_X]/1 mL; ARSENIC TRIOXIDE 15 [hp_X]/1 mL; SEPIA OFFICINALIS JUICE 15 [hp_X]/1 mL; BRYONIA ALBA ROOT 15 [hp_X]/1 mL; ANEMONE PULSATILLA 15 [hp_X]/1 mL; STRYCHNOS NUX-VOMICA SEED 15 [hp_X]/1 mL; PHOSPHORUS 15 [hp_X]/1 mL; ZINC 15 [hp_X]/1 mL; SILICON DIOXIDE 15 [hp_X]/1 mL; TELLURIUM 16 [hp_X]/1 mL
INACTIVE INGREDIENTS: ALCOHOL; WATER

Cataracc 4847L

INDICATIONS & USAGE SECTION

Formulated for symptoms such as blurred vision, light sensitivity and opacities.

DOSAGE & ADMINISTRATION SECTION

Directions: Ages 12 and up, take 6 drops by mouth (ages 0 to 11, give 3 drops) one to four times daily or as directed by a health professional.

OTC - ACTIVE INGREDIENT SECTION

Active Ingredients: Equal parts of Arsenicum album 15x, Bryonia 15x, Calcarea fluorica 15x, Calendula officinalis 15x, Causticum 15x, Conium maculatum 15x, Euphrasia officinalis 15x, Hydrofluoricum acidum 15x, Iodium 15x, Ledum palustre 15x, Naphthalinum 15x, Natrum muriaticum 15x, Nux vomica 15x, Phosphorus 15x, Pulsatilla 15x, Sepia 15x, Silicea 15x, Thiosinaminum 15x, Zincum metallicum 15x, Tellurium metallicum 16x.

OTC - PURPOSE SECTION

Formulated for systems such as blurred vision, light sensitivity, and opacities.

INACTIVE INGREDIENT SECTION

Inactive Ingredients: USP Purified Water; USP Gluten-free, non-GMO, organic cane alcohol 20%.

QUESTIONS SECTION

newtonlabs.net – Questions? 800.448.7256

Newton Laboratories, Inc. FDA Est # 1051203 - Conyers, GA 30013

WARNINGS SECTION

WARNINGS: Keep out of reach of children. Do not use if tamper-evident seal is broken or missing. If symptoms worsen or persist for more than a few days, consult a doctor. If pregnant or breast-feeding, ask a doctor before use.

OTC - PREGNANCY OR BREAST FEEDING SECTION

If pregnant or breast-feeding, ask a doctor before use.

OTC - KEEP OUT OF REACH OF CHILDREN SECTION

Keep out of reach of children.